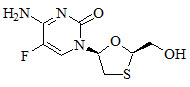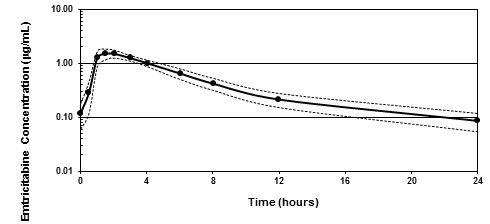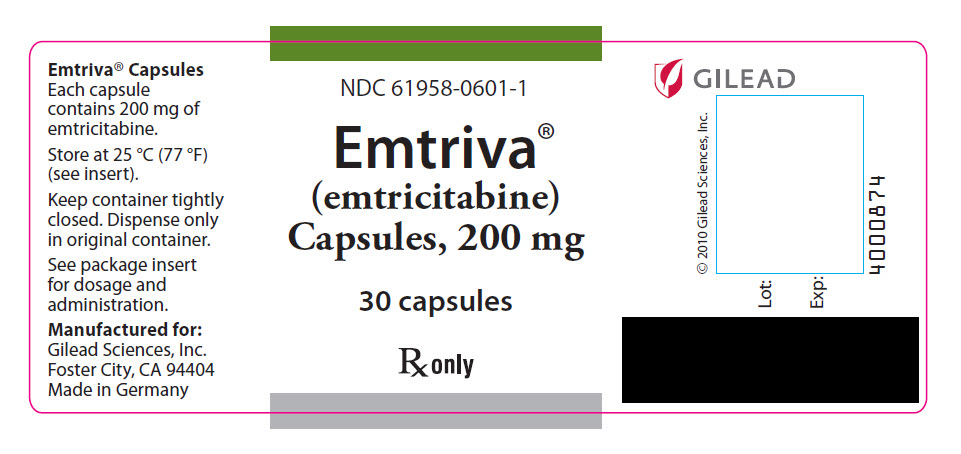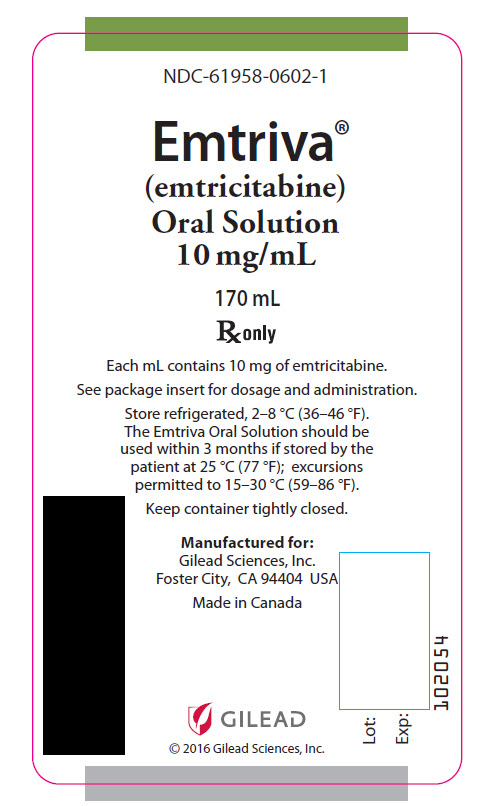 DRUG LABEL: Emtriva
NDC: 61958-0601 | Form: CAPSULE
Manufacturer: Gilead Sciences, Inc.
Category: prescription | Type: HUMAN PRESCRIPTION DRUG LABEL
Date: 20251202

ACTIVE INGREDIENTS: EMTRICITABINE 200 mg/1 1
INACTIVE INGREDIENTS: MICROCRYSTALLINE CELLULOSE; CROSPOVIDONE (120 .MU.M); POVIDONE, UNSPECIFIED; MAGNESIUM STEARATE; WATER; FD&C BLUE NO. 2; TITANIUM DIOXIDE; GELATIN, UNSPECIFIED

HIGHLIGHTS OF PRESCRIBING INFORMATION

These highlights do not include all the information needed to use EMTRIVA safely and effectively. See full prescribing information for EMTRIVA.
EMTRIVA ® (emtricitabine) capsule, for oral use
EMTRIVA ® (emtricitabine) oral solution
Initial U.S. Approval: 2003

WARNING: POSTTREATMENT ACUTE EXACERBATION OF HEPATITIS B

See full prescribing information for complete boxed warning.

Severe acute exacerbations of Hepatitis B (HBV) have been reported in patients coinfected with HIV-1 and HBV who have discontinued EMTRIVA. Hepatic function should be monitored closely in patients coinfected with HIV-1 and HBV who discontinue EMTRIVA. If appropriate, initiation of anti-hepatitis B therapy may be warranted. (5.1)

RECENT MAJOR CHANGES

Dosage and Administration
Testing Prior to Initiation of Treatment with EMTRIVA (2.1) | 12/2018
Warnings and Precautions
Severe Acute Exacerbation of Hepatitis B in Patients Coinfected with HIV-1 and HBV (5.1) | 12/2018
Coadministration with Related Products | Removed 12/2018

1 INDICATIONS AND USAGE

EMTRIVA, a nucleoside analog HIV-1 reverse transcriptase inhibitor, is indicated in combination with other antiretroviral agents for the treatment of HIV-1 infection. (1)

2 DOSAGE AND ADMINISTRATION

- Testing: Prior to or when initiating EMTRIVA test for hepatitis B virus infection. (2.1)
- EMTRIVA may be taken without regard to food. (2.2)
- Adult Patients (18 years of age and older) (2.3):
  - EMTRIVA capsules: One 200 mg capsule administered once daily orally.
  - EMTRIVA oral solution: 240 mg (24 mL) administered once daily orally.
- Pediatric Patients (0–3 months of age) (2.4):
  - EMTRIVA oral solution: 3 mg/kg administered once daily orally.
- Pediatric Patients (3 months through 17 years of age) (2.5):
  - EMTRIVA capsules: For children weighing more than 33 kg who can swallow an intact capsule, one 200 mg capsule administered once daily orally.
  - EMTRIVA oral solution: 6 mg/kg up to a maximum of 240 mg (24 mL) administered once daily orally.
- Dose interval adjustment in adult patients with renal impairment (2.6):

 | Creatinine Clearance (mL/min)
Formulation | ≥50 mL/min | 30–49 mL/min | 15–29 mL/min | <15 mL/min or on hemodialysis [Hemodialysis Patients: If dosing on day of dialysis, give dose after dialysis.]
Capsule (200 mg) | 200 mg every 24 hours | 200 mg every 48 hours | 200 mg every 72 hours | 200 mg every 96 hours
Oral Solution (10 mg/mL) | 240 mg every 24 hours (24 mL) | 120 mg every 24 hours (12 mL) | 80 mg every 24 hours (8 mL) | 60 mg every 24 hours (6 mL)

3 DOSAGE FORMS AND STRENGTHS

- Capsules: 200 mg (3)
- Oral solution: 10 mg per mL (3)

4 CONTRAINDICATIONS

EMTRIVA is contraindicated in patients with previously demonstrated hypersensitivity to any of the components of the products. (4)

5 WARNINGS AND PRECAUTIONS

- Immune reconstitution syndrome: May necessitate further evaluation and treatment. (5.2)
- Lactic acidosis/severe hepatomegaly with steatosis: Discontinue treatment in patients who develop symptoms or laboratory findings suggestive of lactic acidosis or pronounced hepatotoxicity. (5.3)

6 ADVERSE REACTIONS

Most common adverse reactions (incidence ≥10%) are headache, diarrhea, nausea, fatigue, dizziness, depression, insomnia, abnormal dreams, rash, abdominal pain, asthenia, increased cough, and rhinitis. Skin hyperpigmentation was very common (≥10%) in pediatric patients. (6)

To report SUSPECTED ADVERSE REACTIONS, contact Gilead Sciences, Inc. at 1-800-GILEAD-5 or FDA at 1-800-FDA-1088 or www.fda.gov/medwatch.

8 USE IN SPECIFIC POPULATIONS

- Lactation: Breastfeeding is not recommended. (8.2)
- Pediatrics: Dose adjustment based on age and weight. (2.4, 2.5, 12.3)

FULL PRESCRIBING INFORMATION

WARNING: POSTTREATMENT ACUTE EXACERBATION OF HEPATITIS B

Severe acute exacerbations of hepatitis B (HBV) have been reported in patients who are coinfected with HIV-1 and HBV and have discontinued EMTRIVA. Hepatic function should be monitored closely with both clinical and laboratory follow-up for at least several months in patients who are coinfected with HIV-1 and HBV and discontinue EMTRIVA. If appropriate, initiation of anti-hepatitis B therapy may be warranted [see Warnings and Precautions (5.1)].

1 INDICATIONS AND USAGE

EMTRIVA® is indicated in combination with other antiretroviral agents for the treatment of HIV-1 infection.

2 DOSAGE AND ADMINISTRATION

2.1 Testing Prior to Initiation of Treatment with EMTRIVA

Prior to or when initiating EMTRIVA, test patients for hepatitis B virus infection [see Warnings and Precautions (5.1)].

2.2 Recommended Dosage

EMTRIVA is taken by mouth once daily and may be taken without regard to food [see Clinical Pharmacology (12.3)].

2.3 Recommended Dosage in Adult Patients (18 years of age and older)

EMTRIVA capsules: One 200 mg capsule administered once daily orally.

EMTRIVA oral solution: 240 mg (24 mL) administered once daily orally.

2.4 Recommended Dosage in Pediatric Patients (0–3 months of age)

EMTRIVA oral solution: 3 mg per kg administered once daily orally.

2.5 Recommended Dosage in Pediatric Patients (3 months through 17 years of age)

EMTRIVA oral solution: 6 mg per kg up to a maximum of 240 mg (24 mL) administered once daily orally.

EMTRIVA capsules: For pediatric patients weighing more than 33 kg who can swallow an intact capsule, one 200 mg capsule administered once daily orally.

2.6 Dosage Adjustment in Patients with Renal Impairment

Table 1 provides dosage interval adjustment for patients with renal impairment. No dosage adjustment is necessary for patients with mild renal impairment (creatinine clearance 50–80 mL/min). The safety and effectiveness of dose adjustment recommendations in patients with moderate to severe renal impairment (creatinine clearance below 50 mL/min) have not been clinically evaluated. Therefore, clinical response to treatment and renal function should be closely monitored in these patients [see Warnings and Precautions (5.4), Use in Specific Populations (8.6)].

Table 1 Dose Interval Adjustment for Adult Patients with Altered Creatinine Clearance
 | Creatinine Clearance (mL/min)
Formulation | ≥50 mL/min | 30–49 mL/min | 15–29 mL/min | <15 mL/min or on hemodialysis [Hemodialysis Patients: If dosing on day of dialysis, give dose after dialysis.]
Capsule (200 mg) | 200 mg every 24 hours | 200 mg every 48 hours | 200 mg every 72 hours | 200 mg every 96 hours
Oral Solution (10 mg/mL) | 240 mg every 24 hours (24 mL) | 120 mg every 24 hours (12 mL) | 80 mg every 24 hours (8 mL) | 60 mg every 24 hours (6 mL)

There are insufficient data available to make dosage recommendations in pediatric patients with renal impairment.

3 DOSAGE FORMS AND STRENGTHS

EMTRIVA is available as capsules or as an oral solution.

- 200 mg Capsules: 200 mg of emtricitabine (FTC): size 1 hard gelatin capsules with a blue cap and white body, printed with "200 mg" in black on the cap and with "GILEAD" and the corporate logo in black on the body.
- Oral solution: clear, orange to dark orange liquid containing 10 mg of FTC per mL.

4 CONTRAINDICATIONS

EMTRIVA is contraindicated in patients with previously demonstrated hypersensitivity to any of the components of the products.

5 WARNINGS AND PRECAUTIONS

5.1 Severe Acute Exacerbation of Hepatitis B in Patients Coinfected with HIV-1 and HBV

All patients should be tested for the presence of chronic Hepatitis B virus (HBV) before or when initiating EMTRIVA [see Dosage and Administration (2.1)].

Severe acute exacerbations of hepatitis B (e.g., liver decompensation and liver failure) have been reported in patients who are coinfected with HIV-1 and HBV and have discontinued EMTRIVA. Patients who are coinfected with HIV-1 and HBV who discontinue EMTRIVA should be closely monitored with both clinical and laboratory follow-up for at least several months after stopping treatment. If appropriate, initiation of anti-hepatitis B therapy may be warranted, especially in patients with advanced liver disease or cirrhosis, since posttreatment exacerbation of hepatitis may lead to hepatic decompensation and liver failure.

5.2 Immune Reconstitution Syndrome

Immune reconstitution syndrome has been reported in patients treated with combination antiretroviral therapy, including EMTRIVA. During the initial phase of combination antiretroviral treatment, patients whose immune system responds may develop an inflammatory response to indolent or residual opportunistic infections (such as Mycobacterium avium infection, cytomegalovirus, Pneumocystis jirovecii pneumonia [PCP], or tuberculosis), which may necessitate further evaluation and treatment.

Autoimmune disorders (such as Graves' disease, polymyositis, and Guillain-Barré syndrome) have also been reported to occur in the setting of immune reconstitution; however, the time to onset is more variable, and can occur many months after initiation of treatment.

5.3 Lactic Acidosis/Severe Hepatomegaly with Steatosis

Lactic acidosis and severe hepatomegaly with steatosis, including fatal cases, have been reported with the use of nucleoside analogs, including FTC, alone or in combination with other antiretrovirals. Treatment with EMTRIVA should be suspended in any patient who develops clinical or laboratory findings suggestive of lactic acidosis or pronounced hepatotoxicity (which may include hepatomegaly and steatosis even in the absence of marked transaminase elevations).

5.4 Dose Adjustment in Patients with New Onset or Worsening Renal Impairment

Emtricitabine is principally eliminated by the kidney. Reduction of the dosage of EMTRIVA is recommended for patients with impaired renal function [see Dosage and Administration (2.6), Use in Specific Populations (8.6), and Clinical Pharmacology (12.3)].

6 ADVERSE REACTIONS

The following adverse reactions are discussed in other sections of the labeling:

- Severe Acute Exacerbation of Hepatitis B in Patients Coinfected with HIV-1 and HBV [see Warnings and Precautions (5.1)].
- Immune Reconstitution Syndrome [see Warnings and Precautions (5.2)].
- Lactic Acidosis/Severe Hepatomegaly with Steatosis [see Warnings and Precautions (5.3)].

6.1 Clinical Trials Experience

Because clinical trials are conducted under widely varying conditions, adverse reaction rates observed in the clinical trials of a drug cannot be directly compared to rates in the clinical trials of another drug and may not reflect the rates observed in practice.

Adverse Reactions from Clinical Trials Experience in Adults

More than 2,000 adult subjects with HIV-1 infection have been treated with EMTRIVA alone or in combination with other antiretroviral agents for periods of 10 days to 200 weeks in clinical trials.

The most common adverse reactions (incidence greater than or equal to 10%, any severity) identified from any of the three large, controlled clinical trials include headache, diarrhea, nausea, fatigue, dizziness, depression, insomnia, abnormal dreams, rash, abdominal pain, asthenia, increased cough, and rhinitis.

In Trials 301A and 303, the most common adverse reactions that occurred in subjects receiving EMTRIVA with other antiretroviral agents were headache, diarrhea, nausea, and rash, which were generally mild to moderate. Approximately 1% of subjects discontinued participation in the clinical trials due to these events. All adverse reactions were reported with similar frequency in EMTRIVA and control treatment groups except for skin discoloration, which was reported with higher frequency in the EMTRIVA-treated group.

Skin discoloration, manifested by hyperpigmentation on the palms or soles, was generally mild and asymptomatic. The mechanism and clinical significance are unknown.

A summary of EMTRIVA treatment-emergent clinical adverse reactions in Trials 301A and 303 is provided in Table 2.

Table 2 Selected Treatment-Emergent Adverse Reactions (All Grades, Regardless of Causality) Reported in ≥3% of EMTRIVA-Treated Subjects in Either Trial 301A or 303 (0–48 Weeks)
 | 303 |  | 301A
 | EMTRIVA + AZT/d4T + NNRTI/PI (N=294) | 3TC + AZT/d4T + NNRTI/PI (N=146) | EMTRIVA + didanosine + EFV (N=286) | d4T + didanosine + EFV (N=285)
Body as a Whole
Asthenia | 16% | 10% | 12% | 17%
Headache | 13% | 6% | 22% | 25%
Abdominal pain | 8% | 11% | 14% | 17%
Digestive System
Diarrhea | 23% | 18% | 23% | 32%
Nausea | 18% | 12% | 13% | 23%
Vomiting | 9% | 7% | 9% | 12%
Dyspepsia | 4% | 5% | 8% | 12%
Musculoskeletal
Myalgia | 4% | 4% | 6% | 3%
Arthralgia | 3% | 4% | 5% | 6%
Nervous System
Insomnia | 7% | 3% | 16% | 21%
Depressive disorders | 6% | 10% | 9% | 13%
Paresthesia | 5% | 7% | 6% | 12%
Dizziness | 4% | 5% | 25% | 26%
Neuropathy/peripheral neuritis | 4% | 3% | 4% | 13%
Abnormal dreams | 2% | <1% | 11% | 19%
Respiratory
Rhinitis | 18% | 12% | 12% | 10%
Increased cough | 14% | 11% | 14% | 8%
Skin
Rash event [Rash event includes rash, pruritus, maculopapular rash, urticaria, vesiculobullous rash, pustular rash, and allergic reaction.] | 17% | 14% | 30% | 33%
AZT=zidovudine; d4T=stavudine; NNRTI/PI=non-nucleoside reverse transcriptase inhibitor/protease inhibitor; 3TC=lamivudine; EFV=efavirenz.

Laboratory Abnormalities: Laboratory abnormalities in these trials occurred with similar frequency in the EMTRIVA and comparator groups. A summary of Grades 3−4 laboratory abnormalities is provided in Table 3.

Table 3 Treatment-Emergent Grades 3–4 Laboratory Abnormalities Reported in ≥1% of EMTRIVA-Treated Subjects in Either Trial 301A or 303
 | 303 |  | 301A
 | EMTRIVA + AZT/d4T + NNRTI/PI (N=294) | 3TC + AZT/d4T + NNRTI/PI (N=146) | EMTRIVA + Didanosine + EFV (N=286) | d4T + Didanosine + EFV (N=285)
Any ≥ Grade 3 Laboratory Abnormality | 31% | 28% | 34% | 38%
ALT (>5.0 × ULN [ULN = Upper limit of normal]) | 2% | 1% | 5% | 6%
AST (>5.0 × ULN) | 3% | <1% | 6% | 9%
Bilirubin (>2.5 × ULN) | 1% | 2% | <1% | <1%
Creatine kinase (>4.0 × ULN) | 11% | 14% | 12% | 11%
Neutrophils (<750 mm^3) | 5% | 3% | 5% | 7%
Pancreatic amylase (>2.0 × ULN) | 2% | 2% | <1% | 1%
Serum amylase (>2.0 × ULN) | 2% | 2% | 5% | 10%
Serum glucose <40 or >250 mg/dL) | 3% | 3% | 2% | 3%
Serum lipase (>2.0 × ULN) | <1% | <1% | 1% | 2%
Triglycerides (>750 mg/dL) | 10% | 8% | 9% | 6%

In Trial 934, 511 antiretroviral-naïve subjects received efavirenz (EFV) administered in combination with either EMTRIVA + tenofovir disoproxil fumarate (TDF) (N=257) or AZT/3TC (N=254) for 144 weeks. The most common adverse reactions (incidence greater than or equal to 10%, all grades) included diarrhea, nausea, fatigue, headache, dizziness, depression, insomnia, abnormal dreams, and rash. Table 4 provides the treatment-emergent adverse reactions (Grades 2−4) occurring in greater than or equal to 5% of subjects treated in any treatment group.

Table 4 Selected Adverse Reactions [Frequencies of adverse reactions are based on all treatment-emergent adverse events, regardless of relationship to study drug.] (Grades 2–4) Reported in ≥5% in Any Treatment Group in Trial 934 (0–144 Weeks)
 | EMTRIVA + TDF + EFV [From Weeks 96 to 144 of the trial, subjects received TRUVADA ® with EFV in place of EMTRIVA + TDF with EFV.] | AZT/3TC + EFV
 | N=257 | N=254
Fatigue | 9% | 8%
Depression | 9% | 7%
Nausea | 9% | 7%
Diarrhea | 9% | 5%
Dizziness | 8% | 7%
Upper respiratory tract infections | 8% | 5%
Sinusitis | 8% | 4%
Rash event [Rash event includes rash, exfoliative rash, rash generalized, rash macular, rash maculo-papular, rash pruritic, and rash vesicular.] | 7% | 9%
Headache | 6% | 5%
Insomnia | 5% | 7%
Nasopharyngitis | 5% | 3%
Vomiting | 2% | 5%

Laboratory Abnormalities: Laboratory abnormalities observed in Trial 934 were generally consistent with those seen in previous trials (Table 5).

Table 5 Significant Laboratory Abnormalities Reported in ≥1% of Subjects in Any Treatment Group in Trial 934 (0–144 Weeks)
 | EMTRIVA + TDF + EFV [From Weeks 96 to 144 of the trial, subjects received TRUVADA with EFV in place of EMTRIVA + TDF with EFV.] | AZT/3TC + EFV
 | N=257 | N=254
Any ≥ Grade 3 Laboratory Abnormality | 30% | 26%
Fasting Cholesterol (>240 mg/dL) | 22% | 24%
Creatine Kinase (M: >990 U/L) (F: >845 U/L) | 9% | 7%
Serum Amylase (>175 U/L) | 8% | 4%
Alkaline Phosphatase (>550 U/L) | 1% | 0%
AST (M: >180 U/L) (F: >170 U/L) | 3% | 3%
ALT (M: >215 U/L) (F: >170 U/L) | 2% | 3%
Hemoglobin (<8.0 mg/dL) | 0% | 4%
Hyperglycemia (>250 mg/dL) | 2% | 1%
Hematuria (>75 RBC/HPF) | 3% | 2%
Glycosuria (3+) | <1% | 1%
Neutrophils (<750/mm^3) | 3% | 5%
Fasting Triglycerides (>750 mg/dL) | 4% | 2%

Adverse Reactions from Clinical Trials Experience in Pediatric Subjects

Assessment of adverse reactions in pediatric subjects is based on data from Trial 203, an open label, uncontrolled trial of 116 HIV-1 infected subjects who received FTC through 48 weeks. The adverse reaction profile in pediatric subjects was generally comparable to that observed in clinical trials of EMTRIVA in adult subjects [see Adverse Reactions (6.1)]. Hyperpigmentation was more frequent in children. Additional adverse reactions identified from this trial include anemia.

Selected treatment-emergent adverse events, regardless of causality, reported in subjects during 48 weeks of treatment were the following: infection (44%), hyperpigmentation (32%), increased cough (28%), vomiting (23%), otitis media (23%), rash (21%), rhinitis (20%), diarrhea (20%), fever (18%), pneumonia (15%), gastroenteritis (11%), abdominal pain (10%), and anemia (7%). Treatment-emergent Grades 3−4 laboratory abnormalities were experienced by 9% of pediatric subjects, including elevated amylase (>2.0 × ULN) (n=4), decreased neutrophils (<750/mm^3) (n=3), elevated ALT (>5 × ULN) (n=2), elevated CPK (>4 × ULN) (n=2) and one subject each with elevated bilirubin (>3.0 × ULN), elevated GGT (>10 × ULN), elevated lipase (>2.5 × ULN), decreased hemoglobin (<7 g/dL), and decreased glucose (<40 mg/dL).

7 DRUG INTERACTIONS

The potential for drug interactions with EMTRIVA has been studied in combination with AZT, indinavir, d4T, famciclovir, and tenofovir DF (TDF). There were no clinically significant drug interactions for any of these drugs. Drug interactions trials are described elsewhere in the labeling [see Clinical Pharmacology (12.3)].

8 USE IN SPECIFIC POPULATIONS

8.1 Pregnancy

Pregnancy Exposure Registry

There is a pregnancy exposure registry that monitors pregnancy outcomes in women exposed to EMTRIVA during pregnancy. Healthcare providers are encouraged to register patients by calling the Antiretroviral Pregnancy Registry (APR) at 1-800-258-4263.

Risk Summary

Available data from the APR show no increase in the overall risk of major birth defects with first trimester exposure for emtricitabine (FTC) (2.3%) compared with the background rate for major birth defects of 2.7% in a U.S. reference population of the Metropolitan Atlanta Congenital Defects Program (MACDP) (see Data). The rate of miscarriage for individual drugs is not reported in the APR. In the U.S. general population, the estimated background risk of miscarriage in clinically recognized pregnancies is 15–20%.

In animal reproduction studies, no adverse developmental effects were observed when FTC was administered at exposures ≥60 times that of the recommended daily dose of EMTRIVA (see Data).

Data

Human Data

Based on prospective reports to the APR of exposures to FTC-containing regimens during pregnancy resulting in live births (including over 2,700 exposed in the first trimester and over 1,200 exposed in the second/third trimester), there was no increase between FTC and overall birth defects compared with the background birth defect rate of 2.7% in a U.S. reference population of the MACDP. The prevalence of birth defects in live births was 2.4% (95% CI: 1.9% to 3.1%) with first trimester exposure to FTC-containing regimens and 2.3% (95% CI: 1.5% to 3.3%) with the second/third trimester exposure to FTC-containing regimens.

Prospective reports from the APR of overall major birth defects in pregnancies exposed to FTC are compared with a U.S. background major birth defect rate. Methodologic limitations of the APR include the use of MACDP as the external comparator group. Limitations of using an external comparator include differences in methodology and populations, as well as confounding due to the underlying disease.

Additionally, published observational studies on FTC exposure in pregnancy have not shown an increased risk for major malformations.

Animal Data

FTC was administered orally to pregnant mice (at 0, 250, 500, or 1,000 mg/kg/day), and rabbits (at 0, 100, 300, or 1,000 mg/kg/day) through organogenesis (on gestation days 6 through 15, and 7 through 19, respectively). No significant toxicological effects were observed in embryo-fetal toxicity studies performed with FTC in mice at exposures (AUC) approximately 60 times higher and in rabbits at approximately 120 times higher than human exposures at the recommended daily dose. In a pre/postnatal development study in mice, FTC was administered orally at doses up to 1,000 mg/kg/day; no significant adverse effects directly related to drug were observed in the offspring exposed daily from before birth (in utero) through sexual maturity at daily exposures (AUC) of approximately 60 times higher than human exposures at the recommended daily dose.

8.2 Lactation

Risk Summary

The Centers for Disease Control and Prevention recommend that HIV-1 infected mothers not breastfeed their infants to avoid risking postnatal transmission of HIV-1.

Based on published data, FTC has been shown to be present in human breast milk. It is not known if FTC affects milk production or has effects on the breastfed child.

Because of the potential for: (1) HIV transmission (in HIV-negative infants); (2) developing viral resistance (in HIV-positive infants); and (3) adverse reactions in a breastfed infant similar to those seen in adults, instruct mothers not to breastfeed if they are taking EMTRIVA.

8.4 Pediatric Use

The safety and efficacy of FTC in patients between 3 months and 21 years of age is supported by data from three open-label, nonrandomized clinical trials in which FTC was administered to 169 HIV-1 infected treatment-naïve and experienced (defined as virologically suppressed on a 3TC containing regimen for which FTC was substituted for 3TC) subjects [see Clinical Studies (14.4)].

The pharmacokinetics of FTC were studied in 20 neonates born to HIV-1 positive mothers [see Clinical Studies (14.4)]. All neonates were HIV-1 negative at the end of the trial; the efficacy of FTC in preventing or treating HIV-1 could not be determined.

8.5 Geriatric Use

Clinical trials of EMTRIVA did not include sufficient numbers of subjects aged 65 years and over to determine whether they respond differently from younger subjects. In general, dose selection for the elderly patient should be cautious, keeping in mind the greater frequency of decreased hepatic, renal, or cardiac function, and of concomitant disease or other drug therapy.

8.6 Renal Impairment

Modify the dose or dosing interval for EMTRIVA in patients with creatinine clearance below 50 mL/min or in patients with end stage renal disease requiring dialysis [see Dosage and Administration (2.6)].

10 OVERDOSAGE

If overdose occurs, the patient should be monitored for evidence of toxicity, and standard supportive treatment applied as necessary.

Hemodialysis treatment removes approximately 30% of the FTC dose over a 3-hour dialysis period starting within 1.5 hours of FTC dosing (blood flow rate of 400 mL/min and a dialysate flow rate of 600 mL/min). It is not known whether FTC can be removed by peritoneal dialysis.

11 DESCRIPTION

EMTRIVA is the brand name of emtricitabine (FTC), a synthetic nucleoside analog with activity against human immunodeficiency virus type 1 (HIV-1) reverse transcriptase.

The chemical name of FTC is 5-fluoro-1-(2R,5S)-[2-(hydroxymethyl)-1,3-oxathiolan-5-yl]cytosine. Emtricitabine is the (-) enantiomer of a thio analog of cytidine, which differs from other cytidine analogs in that it has a fluorine in the 5-position.

It has a molecular formula of C8H10FN3O3S and a molecular weight of 247.24. It has the following structural formula:

Emtricitabine is a white to off-white powder with a solubility of approximately 112 mg/mL in water at 25 °C. The partition coefficient (log P) for FTC is −0.43 and the pKa is 2.65.

EMTRIVA is available as capsules or as an oral solution.

EMTRIVA capsules are for oral administration. Each capsule contains 200 mg of FTC and the inactive ingredients crospovidone, magnesium stearate, microcrystalline cellulose, povidone, titanium dioxide, gelatin, and FD&C blue No. 2.

EMTRIVA oral solution is for oral administration. One milliliter (1 mL) of EMTRIVA oral solution contains 10 mg of FTC in an aqueous solution with the following inactive ingredients: cotton candy flavor, FD&C yellow No. 6, edetate disodium, methylparaben and propylparaben (added as preservatives), sodium phosphate (monobasic), propylene glycol, water, and xylitol (added as a sweetener). Sodium hydroxide and hydrochloric acid may be used to adjust pH.

12 CLINICAL PHARMACOLOGY

12.1 Mechanism of Action

Emtricitabine is an antiretroviral drug [see Microbiology (12.4)].

12.3 Pharmacokinetics

Adults

The pharmacokinetic properties of FTC were evaluated in healthy subjects and HIV-1-infected subjects. Emtricitabine pharmacokinetics are similar between these populations.

Figure 1 shows the mean steady-state plasma FTC concentration-time profile in 20 HIV-1-infected subjects receiving EMTRIVA capsules.

Figure 1 Mean (± 95% CI) Steady-State Plasma FTC Concentrations in HIV-1 Infected Adults (N=20)

Absorption

Emtricitabine is rapidly and extensively absorbed following oral administration, with peak plasma concentrations occurring at 1–2 hours postdose. Following multiple dose oral administration of EMTRIVA capsules to 20 HIV-1 infected subjects, the (mean ± SD) steady-state plasma FTC peak concentration (Cmax) was 1.8 ± 0.7 µg/mL and the area-under the plasma concentration-time curve over a 24-hour dosing interval (AUC) was 10.0 ± 3.1 µg∙hr/mL. The mean steady-state plasma trough concentration at 24 hours postdose was 0.09 µg/mL. The mean absolute bioavailability of EMTRIVA capsules was 93%, while the mean absolute bioavailability of EMTRIVA oral solution was 75%. The relative bioavailability of EMTRIVA oral solution was approximately 80% of EMTRIVA capsules.

The multiple dose pharmacokinetics of FTC are dose proportional over a dose range of 25–200 mg.

Distribution

In vitro binding of FTC to human plasma proteins was less than 4% and independent of concentration over the range of 0.02–200 µg/mL. At peak plasma concentration, the mean plasma to blood drug concentration ratio was ~1.0 and the mean semen to plasma drug concentration ratio was ~4.0.

Metabolism

Following administration of radiolabelled FTC, complete recovery of the dose was achieved in urine (~86%) and feces (~14%). Thirteen percent (13%) of the dose was recovered in urine as three putative metabolites. The biotransformation of FTC includes oxidation of the thiol moiety to form the 3'-sulfoxide diastereomers (~9% of dose) and conjugation with glucuronic acid to form 2'-O-glucuronide (~4% of dose). No other metabolites were identifiable.

Elimination

The plasma FTC half-life is approximately 10 hours. The renal clearance of FTC is greater than the estimated creatinine clearance, suggesting elimination by both glomerular filtration and active tubular secretion. There may be competition for elimination with other compounds that are also renally eliminated.

Effects of Food on Oral Absorption

EMTRIVA capsules and oral solution may be taken with or without food. Emtricitabine systemic exposure (AUC) was unaffected while Cmax decreased by 29% when EMTRIVA capsules were administered with food (an approximately 1000 kcal high-fat meal). Emtricitabine systemic exposure (AUC) and Cmax were unaffected when 200 mg EMTRIVA oral solution was administered with either a high-fat or low-fat meal.

Specific Populations

Geriatric Patients

The pharmacokinetics of FTC have not been fully evaluated in the elderly (65 years of age and older).

Pediatric Patients

The pharmacokinetics of FTC at steady state were determined in 77 HIV-1 infected pediatric subjects, and the pharmacokinetic profile was characterized in four age groups (Table 6). The FTC exposure achieved in pediatric subjects receiving a daily dose of 6 mg/kg up to a maximum of 240 mg oral solution or a 200-mg capsule is similar to exposures achieved in adult subjects receiving a once-daily dose of 200 mg.

The pharmacokinetics of FTC were studied in 20 neonates born to HIV-1 positive mothers. Each mother received prenatal and intrapartum combination antiretroviral therapy. Neonates received up to 6 weeks of AZT prophylactically after birth. The neonates were administered two short courses of FTC oral solution (each 3 mg/kg once daily × 4 days) during the first 3 months of life. The AUC observed in neonates who received a daily dose of 3 mg/kg of FTC was similar to the AUC observed in pediatric subjects aged 3 months to 17 years who received a daily dose of FTC as a 6 mg/kg oral solution up to 240 mg or as a 200-mg capsule (Table 6).

Table 6 Mean ± SD Pharmacokinetic Parameters by Age Groups for Pediatric Subjects and Neonates Receiving EMTRIVA Capsules or Oral Solution
 | HIV-1-exposed Neonates | HIV-1 Infected Pediatric Subjects
Age | 0–3 mo (N=20) [Two pharmacokinetic evaluations were conducted in 20 neonates over the first 3 months of life. Median (range) age of infant on day of pharmacokinetic evaluation was 26 (5–81) days.] | 3–24 mo (N=14) | 25 mo–6 yr (N=19) | 7–12yr (N=17) | 13–17 yr (N=27)
Formulation
Capsule (n) | 0 | 0 | 0 | 10 | 26
Oral Solution (n) | 20 | 14 | 19 | 7 | 1
Dose (mg/kg) [Mean (range).] | 3.1 (2.9–3.4) | 6.1 (5.5–6.8) | 6.1 (5.6–6.7) | 5.6 (3.1–6.6) | 4.4 (1.8–7.0)
Cmax (µg/mL) | 1.6 ± 0.6 | 1.9 ± 0.6 | 1.9 ± 0.7 | 2.7 ± 0.8 | 2.7 ± 0.9
AUC (µg∙hr/mL) | 11.0 ± 4.2 | 8.7 ± 3.2 | 9.0 ± 3.0 | 12.6 ± 3.5 | 12.6 ± 5.4
T1/2 (hr) | 12.1 ± 3.1 | 8.9 ± 3.2 | 11.3 ± 6.4 | 8.2 ± 3.2 | 8.9 ± 3.3

Gender

FTC pharmacokinetics are similar in adult male and female subjects.

Race

No pharmacokinetic differences due to race have been identified.

Patients with Renal Impairment

The pharmacokinetics of FTC are altered in subjects with renal impairment [see Warnings and Precautions (5.4)]. In adult subjects with creatinine clearance below 50 mL/min or with end-stage renal disease (ESRD) requiring dialysis, Cmax and AUC of FTC were increased (Table 7). The effects of renal impairment on FTC pharmacokinetics in pediatric patients are not known.

Table 7 Pharmacokinetic Parameters (Mean ± SD) of FTC in Adult Subjects with Varying Degrees of Renal Function
Creatinine Clearance (mL/min) | >80 (N=6) | 50–80 (N=6) | 30–49 (N=6) | <30 (N=5) | ESRD [ESRD subjects requiring dialysis] <30 (N=5)
Baseline creatinine clearance (mL/min) | 107 ± 21 | 59.8 ± 6.5 | 40.9 ± 5.1 | 22.9 ± 5.3 | 8.8 ± 1.4
Cmax (µg/mL) | 2.2 ± 0.6 | 3.8 ± 0.9 | 3.2 ± 0.6 | 2.8 ± 0.7 | 2.8 ± 0.5
AUC (µg∙hr/mL) | 11.8 ± 2.9 | 19.9 ± 1.2 | 25.1 ± 5.7 | 33.7± 2.1 | 53.2 ± 9.9
CL/F (mL/min) | 302 ± 94 | 168 ± 10 | 138 ± 28 | 99 ± 6 | 64 ± 12
CLr (mL/min) | 213 ± 89 | 121 ± 39 | 69 ± 32 | 30 ± 11 | NA [NA = Not Applicable]

Patients with Hepatic Impairment

The pharmacokinetics of FTC have not been studied in subjects with hepatic impairment; however, FTC is not significantly metabolized by liver enzymes, so the impact of liver impairment should be limited.

Assessment of Drug Interactions

At concentrations up to 14-fold higher than those observed in vivo, FTC did not inhibit in vitro drug metabolism mediated by any of the following human CYP isoforms: CYP1A2, CYP2A6, CYP2B6, CYP2C9, CYP2C19, CYP2D6, and CYP3A4. FTC did not inhibit the enzyme responsible for glucuronidation (uridine-5'-disphosphoglucuronyl transferase). Based on the results of these in vitro experiments and the known elimination pathways of FTC, the potential for CYP-mediated interactions involving FTC with other medicinal products is low.

EMTRIVA has been evaluated in healthy volunteers in combination with TDF, AZT, indinavir, famciclovir, and d4T. Tables 8 and 9 summarize the pharmacokinetic effects of coadministered drug on FTC pharmacokinetics and effects of FTC on the pharmacokinetics of coadministered drug.

Table 8 Drug Interactions: Change in Pharmacokinetic Parameters for FTC in the Presence of the Coadministered Drug [All interaction trials conducted in healthy volunteers.]
Coadministered Drug | Dose of Coadministered Drug (mg) | FTC Dose (mg) | N | % Change of FTC Pharmacokinetic Parameters [↑ = Increase; ⇔ = No Effect; NA = Not Applicable] (90% CI)
Coadministered Drug | Dose of Coadministered Drug (mg) | FTC Dose (mg) | N | Cmax | AUC | Cmin
Famciclovir | 500 × 1 | 200 × 1 | 12 | ⇔ | ⇔ | NA
Indinavir | 800 × 1 | 200 × 1 | 12 | ⇔ | ⇔ | NA
Stavudine | 40 × 1 | 200 × 1 | 6 | ⇔ | ⇔ | NA
Tenofovir DF | 300 once daily × 7 days | 200 once daily × 7 days | 17 | ⇔ | ⇔ | ↑ 20 (↑ 12 to ↑ 29)
Zidovudine | 300 twice daily × 7 days | 200 once daily × 7 days | 27 | ⇔ | ⇔ | ⇔

Table 9 Drug Interactions: Change in Pharmacokinetic Parameters for Coadministered Drug in the Presence of FTC [All interaction trials conducted in healthy volunteers.]
Coadministered Drug | Dose of Coadministered Drug (mg) | FTC Dose (mg) | N | % Change of Coadministered Drug Pharmacokinetic Parameters [↑ = Increase; ⇔ = No Effect; NA = Not Applicable] (90% CI)
Coadministered Drug | Dose of Coadministered Drug (mg) | FTC Dose (mg) | N | Cmax | AUC | Cmin
Famciclovir | 500 × 1 | 200 × 1 | 12 | ⇔ | ⇔ | NA
Indinavir | 800 × 1 | 200 × 1 | 12 | ⇔ | ⇔ | NA
Stavudine | 40 × 1 | 200 × 1 | 6 | ⇔ | ⇔ | NA
Tenofovir DF | 300 once daily × 7 days | 200 once daily × 7 days | 17 | ⇔ | ⇔ | ⇔
Zidovudine | 300 twice daily × 7 days | 200 once daily × 7 days | 27 | ↑ 17 (↑ 0 to ↑ 38) | ↑ 13 (↑ 5 to↑ 20) | ⇔

12.4 Microbiology

Mechanism of Action

FTC, a synthetic nucleoside analog of cytidine, is phosphorylated by cellular enzymes to form emtricitabine 5'-triphosphate (FTC-TP), which inhibits the activity of the HIV-1 reverse transcriptase (RT) by competing with the natural substrate deoxycytidine 5'-triphosphate and by being incorporated into nascent viral DNA resulting in chain termination. FTC-TP is a weak inhibitor of mammalian DNA polymerases α, β, ε, and mitochondrial DNA polymerase γ.

Antiviral Activity

The antiviral activity of FTC against laboratory and clinical isolates of HIV-1 was assessed in lymphoblastoid cell lines, the MAGI-CCR5 cell line, and peripheral blood mononuclear cells. The 50% effective concentration (EC50) values for FTC were in the range of 0.0013–0.64 µM (0.0003–0.158 µg/mL). The median EC50, range, and number of isolates for the laboratory isolates were 0.07, 0.009−0.62, 10; 0.011, 0.002−0.03, 12; 0.055, 0.0015−0.09, 4 respectively for lymphoblastoid, PBMC, and reporter cells. The median EC50, range, and number of isolates for the clinical isolates were 0.05, 0.0105−0.64, 15; 0.015, 0.004−0.028, 6 respectively for lymphoblastoid cells and PBMCs. No antagonism was observed in drug combination studies of emtricitabine with nucleoside reverse transcriptase inhibitors (NRTIs) (abacavir, lamivudine, stavudine, tenofovir, zidovudine), non-nucleoside reverse transcriptase inhibitors (NNRTIs) (delavirdine, efavirenz, nevirapine), and protease inhibitors (amprenavir, nelfinavir, ritonavir, saquinavir). FTC displayed antiviral activity in cell culture against HIV-1 clades A, B, C, D, E, F, and G (EC50 values ranged from 0.007–0.075 µM) and showed strain-specific activity against HIV-2 (EC50 values ranged from 0.007–1.5 µM in PBMCs and MAGI cells).

Resistance

FTC-resistant isolates of HIV-1 have been selected in cell culture and in vivo. Genotypic analysis of these isolates showed that the reduced susceptibility to FTC was associated with a valine or isoleucine (M184V/I) substitution in the HIV-1 RT.

FTC-resistant isolates of HIV-1 have been recovered from some subjects treated with FTC alone or in combination with other antiretroviral agents. In a clinical trial of treatment-naïve subjects treated with EMTRIVA, didanosine, and efavirenz (EFV) [see Clinical Studies (14.2)], viral isolates from 37.5% of subjects with virologic failure showed reduced susceptibility to FTC. Genotypic analysis of these isolates showed that the resistance was due to M184V/I substitutions in the HIV-1 RT.

In a clinical trial of treatment-naïve subjects treated with either EMTRIVA, TDF, and EFV or AZT/3TC and EFV [see Clinical Studies (14.2)], resistance analysis was performed on HIV-1 isolates from all confirmed virologic failure subjects with greater than 400 copies/mL of HIV-1 RNA at Week 144 or early discontinuation. Development of EFV resistance-associated substitutions occurred most frequently and was similar between the treatment arms. The M184V amino acid substitution, associated with resistance to EMTRIVA and 3TC, was observed in 2/19 analyzed subject isolates in the EMTRIVA + TDF group and in 10/29 analyzed subject isolates in the AZT/3TC group. Through 144 weeks of Trial 934, no subjects have developed a detectable K65R substitution in their HIV-1 as analyzed through standard genotypic analysis.

Cross Resistance

Cross-resistance among certain NRTIs has been recognized. FTC-resistant isolates (M184V/I) were cross-resistant to 3TC but retained susceptibility in cell culture to AZT, didanosine, d4T, and tenofovir, and to NNRTIs (delavirdine, EFV, and nevirapine). HIV-1 isolates containing the K65R substitution, selected in vivo by abacavir, didanosine, and tenofovir, demonstrated reduced susceptibility to inhibition by FTC. Viruses harboring substitutions conferring reduced susceptibility to AZT and d4T (M41L, D67N, K70R, L210W, T215Y/F, K219Q/E) or didanosine (L74V) remained sensitive to FTC. HIV-1 containing the K103N substitution associated with resistance to NNRTIs was susceptible to FTC.

13 NONCLINICAL TOXICOLOGY

13.1 Carcinogenesis, Mutagenesis, Impairment of Fertility

In long-term oral carcinogenicity studies of FTC, no drug-related increases in tumor incidence were found in mice at doses up to 750 mg/kg/day (26 times the human systemic exposure at the therapeutic dose of 200 mg/day) or in rats at doses up to 600 mg/kg/day (31 times the human systemic exposure at the therapeutic dose).

Emtricitabine was not genotoxic in the reverse mutation bacterial test (Ames test) or mouse lymphoma or mouse micronucleus assays.

Emtricitabine did not affect fertility in male rats at approximately 140-fold or in male and female mice at approximately 60-fold higher exposures (AUC) than in humans given the recommended 200 mg daily dose. Fertility was normal in the offspring of mice exposed daily from before birth (in utero) through sexual maturity at daily exposures (AUC) of approximately 60-fold higher than human exposures at the recommended 200 mg daily dose.

14 CLINICAL STUDIES

14.1 Overview of Clinical Trials

The efficacy and safety of EMTRIVA were evaluated in the trials summarized in Table 10.

Table 10 Trials Conducted with EMTRIVA in Adult and Pediatric Subjects
Trial | Population | Trial Arms (N) [Randomized and dosed.] | Timepoint (Weeks)
Trial 934 [Randomized, open-label, active-controlled trial.] (NCT00112047) | HIV-1 treatment-naïve adults | EMTRIVA+TDF+EFV (227) AZT/3TC+EFV (229) | 144
Trial 301A [Randomized, double-blind, active-controlled trial.] (NCT00006208) | HIV-1 treatment-naïve adults | EMTRIVA+didanosine+EFV (286) d4T+didanosine+EFV (285) | 48
Trial 303 (NCT00002416) | HIV-1 treatment-experienced adults | EMTRIVA+AZT/d4T+NNRTI/PI (294) 3TC+AZT/d4T+NNRTI/PI (146) | 48
Trial 202 [Nonrandomized, open-label trial.] (NCT00016718) | HIV-1 treatment-naïve and experienced pediatrics | EMTRIVA+didanosine+EFV (43) | 48
Trial 203 (NCT00743340) | HIV-1 treatment-naïve and experienced pediatrics | EMTRIVA+d4T+lopinavir/ritonavir (116) | 48
Trial 211 (NCT00642291) | HIV-1 treatment-naïve and experienced pediatrics | EMTRIVA+didanosine+EFV (16) | 48

14.2 Clinical Trial Results in Treatment-Naïve Adults

Trial 934

Data through 144 weeks are reported for Trial 934, a randomized, open-label, active-controlled multicenter clinical trial comparing EMTRIVA + TDF administered in combination with EFV versus AZT/3TC fixed-dose combination administered in combination with EFV in 511 antiretroviral-naïve subjects. From Weeks 96 to 144 of the trial, subjects received FTC/TDF fixed-dose combination with EFV in place of EMTRIVA + TDF with EFV. Subjects had a mean age of 38 years (range 18–80); 86% were male, 59% were Caucasian, and 23% were Black. The mean baseline CD4+ cell count was 245 cells/mm^3 (range 2–1191) and median baseline plasma HIV-1 RNA was 5.01 log10 copies/mL (range 3.56–6.54). Subjects were stratified by baseline CD4+ cell count (< or ≥200 cells/mm^3); 41% had CD4+ cell counts <200 cells/mm^3 and 51% of subjects had baseline viral loads >100,000 copies/mL. Table 11 provides treatment outcomes through 48 and 144 weeks for those subjects who did not have EFV resistance at baseline.

Table 11 Virologic Outcomes of Randomized Treatment at Week 48 and 144 (Trial 934)
Outcomes | Week 48 |  | Week 144
Outcomes | EMTRIVA+TDF+EFV (N=244) | AZT/3TC+EFV (N=243) | EMTRIVA+TDF+EFV (N=227) [Subjects who were responders at Week 48 or Week 96 (HIV-1 RNA <400 copies/mL) but did not consent to continue in the trial after Week 48 or Week 96 were excluded from analysis.] | AZT/3TC+EFV (N=229)
Responder [Subjects achieved and maintained confirmed HIV-1 RNA <400 copies/mL through Weeks 48 and 144.] | 84% | 73% | 71% | 58%
Virologic failure [Includes confirmed viral rebound and failure to achieve confirmed <400 copies/mL through Weeks 48 and 144.] | 2% | 4% | 3% | 6%
Rebound | 1% | 3% | 2% | 5%
Never suppressed | 0% | 0% | 0% | 0%
Change in antiretroviral regimen | 1% | 1% | 1% | 1%
Death | <1% | 1% | 1% | 1%
Discontinued due to adverse event | 4% | 9% | 5% | 12%
Discontinued for other reasons [Includes lost to follow-up, subject withdrawal, noncompliance, protocol violation and other reasons.] | 10% | 14% | 20% | 22%

Through Week 48, 84%, and 73% of subjects in the EMTRIVA + TDF group and the AZT/3TC group, respectively, achieved and maintained HIV-1 RNA <400 copies/mL (71% and 58% through Week 144). The difference in the proportion of subjects who achieved and maintained HIV-1 RNA <400 copies/mL through 48 weeks largely results from the higher number of discontinuations due to adverse events and other reasons in the AZT/3TC group in this open-label trial. In addition, 80% and 70% of subjects in the EMTRIVA + TDF group and the AZT/3TC group, respectively, achieved and maintained HIV-1 RNA <50 copies/mL through Week 48 (64% and 56% through Week 144). The mean increase from baseline in CD4+ cell count was 190 cells/mm^3 in the EMTRIVA + TDF group and 158 cells/mm^3 in the AZT/3TC group at Week 48 (312 and 271 cells/mm^3 at Week 144).

Through 48 weeks, 7 subjects in the EMTRIVA + TDF group and 5 subjects in the AZT/3TC group experienced a new CDC Class C event (10 and 6 subjects through 144 weeks).

Trial 301A

Trial 301A was a 48-week double-blind, active-controlled, multicenter clinical trial comparing EMTRIVA (200 mg once daily) administered in combination with didanosine and EFV versus d4T, didanosine, and EFV in 571 antiretroviral naïve adult subjects. Subjects had a mean age of 36 years (range 18–69); 85% were male, 52% Caucasian, 16% African-American, and 26% Hispanic. Subjects had a mean baseline CD4+ cell count of 318 cells/mm^3 (range 5–1317) and a median baseline plasma HIV-1 RNA of 4.9 log10 copies/mL (range 2.6–7.0). Thirty-eight percent of subjects had baseline viral loads >100,000 copies/mL and 31% had CD4+ cell counts <200 cells/mL. Table 12 provides treatment outcomes through 48 weeks.

Table 12 Virologic Outcomes of Randomized Treatment at Week 48 (Trial 301A)
Outcomes | EMTRIVA+ Didanosine+ EFV (N=286) | d4T+ Didanosine+ EFV (N=285)
Responder [Subjects achieved and maintained confirmed HIV RNA <400 copies/mL (<50 copies/mL) through Week 48.] | 81% (78%) | 68% (59%)
Virologic Failure [Includes subjects who failed to achieve virologic suppression or rebounded after achieving virologic suppression.] | 3% | 11%
Death | 0% | <1%
Discontinuation Due to Adverse Event | 7% | 13%
Discontinuation for Other Reasons [Includes lost to follow-up, subject withdrawal, non-compliance, protocol violation, and other reasons.] | 9% | 8%

The mean increase from baseline in CD4+ cell count was 168 cells/mm^3 for the EMTRIVA arm and 134 cells/mm^3 for the d4T arm.

Through 48 weeks, 5 subjects (1.7%) in the EMTRIVA group experienced a new CDC Class C event compared to 7 subjects (2.5%) in the d4T group.

14.3 Clinical Trial Results in Treatment-Experienced Adults

Trial 303

Trial 303 was a 48-week, open-label, active-controlled, multicenter clinical trial comparing EMTRIVA (200 mg once daily) to 3TC, in combination with d4T or AZT and a protease inhibitor or NNRTI in 440 adult subjects who were on a 3TC-containing triple-antiretroviral drug regimen for at least 12 weeks prior to trial entry and had HIV-1 RNA ≤400 copies/mL.

Subjects were randomized 1:2 to continue therapy with 3TC (150 mg twice daily) or to switch to EMTRIVA (200 mg once daily). All subjects were maintained on their stable background regimen. Subjects had a mean age of 42 years (range 22–80); 86% were male, 64% Caucasian, 21% African-American, and 13% Hispanic. Subjects had a mean baseline CD4+ cell count of 527 cells/mm^3 (range 37–1909), and a median baseline plasma HIV-1 RNA of 1.7 log10 copies/mL (range 1.7–4.0).

The median duration of prior antiretroviral therapy was 27.6 months. Table 13 provides treatment outcomes through 48 weeks.

Table 13 Virologic Outcomes of Randomized Treatment at Week 48 (Trial 303)
Outcomes | EMTRIVA+ AZT/d4T+ NNRTI/PI (N=294) | 3TC+ AZT/d4T+ NNRTI/PI (N=146)
Responder [Subjects achieved and maintained confirmed HIV RNA <400 copies/mL (<50 copies/mL) through Week 48.] | 77% (67%) | 82% (72%)
Virologic Failure [Includes subjects who failed to achieve virologic suppression or rebounded after achieving virologic suppression.] | 7% | 8%
Death | 0% | <1%
Discontinuation Due to Adverse Event | 4% | 0%
Discontinuation for Other Reasons [Includes lost to follow-up, subject withdrawal, non-compliance, protocol violation, and other reasons.] | 12% | 10%

The mean increase from baseline in CD4+ cell count was 29 cells/mm^3 for the EMTRIVA arm and 61 cells/mm^3 for the 3TC arm.

Through 48 weeks, in the EMTRIVA group 2 subjects (0.7%) experienced a new CDC Class C event compared to 2 subjects (1.4%) in the 3TC group.

14.4 Clinical Trial Results in Pediatrics

In three open-label, nonrandomized clinical trials, FTC was administered to 169 HIV-1 infected treatment-naïve and experienced (defined as virologically suppressed on a 3TC-containing regimen for which FTC was substituted for 3TC) subjects between 3 months and 21 years of age. Subjects received once-daily EMTRIVA oral solution (6 mg/kg to a maximum of 240 mg/day) or EMTRIVA capsules (a single 200 mg capsule once daily) in combination with at least two other antiretroviral agents.

Subjects had a mean age of 7.9 years (range 0.3–21); 49% were male, 15% Caucasian, 61% Black, and 24% Hispanic. Subjects had a median baseline HIV-1 RNA of 4.6 log10 copies/mL (range 1.7–6.4) and a mean baseline CD4+ cell count of 745 cells/mm^3 (range 2–2650). Through 48 weeks of therapy, the overall proportion of subjects who achieved and sustained an HIV-1 RNA <400 copies/mL was 86%, and <50 copies/mL was 73%. The mean increase from baseline in CD4+ cell count was 232 cells/mm^3 (−945, +1512). The adverse reaction profile observed during these clinical trials was similar to that of adult subjects, with the exception of the occurrence of anemia and higher frequency of hyperpigmentation in children [see Adverse Reactions (6.1)].

The pharmacokinetics of FTC were studied in 20 neonates born to HIV-1 positive mothers. Each mother received prenatal and intrapartum combination antiretroviral therapy. Neonates received up to 6 weeks of AZT prophylactically after birth. The neonates were administered two short courses of FTC oral solution (each 3 mg/kg once daily × 4 days) during the first 3 months of life. FTC exposures in neonates were similar to the exposures achieved in subjects aged 3 months to 17 years [see Clinical Pharmacology (12.3)]. During the two short dosing periods on FTC, there were no safety issues identified in the treated neonates. All neonates were HIV-1 negative at the end of the trial; the efficacy of FTC in preventing or treating HIV-1 could not be determined.

16 HOW SUPPLIED/STORAGE AND HANDLING

EMTRIVA capsules are available in bottles containing 30 capsules with child-resistant closure as follows:

200 mg of FTC capsules are size 1 hard gelatin capsules with a blue cap and white body and printed with "200 mg" in black on the cap and with "GILEAD" and the corporate logo in black on the body (NDC 61958–0601–1).

- Store EMTRIVA capsules at 25 °C (77 °F); excursions permitted to 15–30 °C (59–86 °F).
- Dispense only in original container. Keep container tightly closed.

EMTRIVA oral solution is a clear, orange to dark orange liquid containing 10 mg/mL of FTC and is available in unit of use plastic, amber bottles containing 170 mL of oral solution closed with a child resistant closure, and packaged with a marked dosing cup (NDC 61958–0602–1).

STORAGE AND HANDLING

Store EMTRIVA oral solution refrigerated at 2–8 °C (36–46 °F). EMTRIVA oral solution should be used within 3 months if stored by the patient at 25 °C (77 °F); excursions permitted to 15–30 °C (59–86 °F).

- Keep container tightly closed.

17 PATIENT COUNSELING INFORMATION

Advise the patient to read the FDA-approved patient labeling (Patient Information).

Severe Acute Exacerbation of Hepatitis B in Patients Coinfected with HIV-1 and HBV

Inform patients that severe acute exacerbations of hepatitis B have been reported in patients who are coinfected with HIV-1 and hepatitis B virus (HBV) who have discontinued EMTRIVA. Advise patients not to discontinue EMTRIVA without first informing their healthcare provider. All patients should be tested for HBV infection before or when starting EMTRIVA and those who are infected with HBV need close medical follow-up for several months after stopping EMTRIVA to monitor for exacerbations of hepatitis [see Warnings and Precautions (5.1)].

Immune Reconstitution Syndrome

Inform patients that in some patients with advanced HIV infection (AIDS), signs and symptoms of inflammation from previous infections may occur soon after anti-HIV treatment is started. It is believed that these symptoms are due to an improvement in the body's immune response, enabling the body to fight infections that may have been present with no obvious symptoms. Advise patients to inform their healthcare provider immediately of any symptoms of infection [see Warnings and Precautions (5.2)].

Lactic Acidosis and Severe Hepatomegaly

Inform patients that lactic acidosis and severe hepatomegaly with steatosis, including fatal cases, have been reported. Treatment with EMTRIVA should be suspended in any patient who develops clinical symptoms suggestive of lactic acidosis or pronounced hepatotoxicity [see Warnings and Precautions (5.3)].

Pregnancy Registry

Inform patients that there is an antiretroviral pregnancy registry to monitor fetal outcomes of pregnant women exposed to EMTRIVA [see Use in Specific Populations (8.1)].

Lactation

Instruct mothers not to breastfeed if they are taking EMTRIVA because of the risk of passing the HIV-1 virus to the baby [see Use in Specific Populations (8.2)].

© 2018 Gilead Sciences, Inc. All rights reserved.

Manufactured for and distributed by:

Gilead Sciences, Inc.
Foster City, CA 94404

EMTRIVA and TRUVADA are trademarks of Gilead Sciences, Inc., or its related companies. All other trademarks referenced herein are the property of their respective owners.

21-500-896-GS-019

Patient Information
EMTRIVA® (em-treev'-ah)
(emtricitabine)
capsules and oral solution

What is the most important information I should know about EMTRIVA?

EMTRIVA can cause serious side effects, including:

- Worsening of Hepatitis B virus infection (HBV). Your healthcare provider will test you for HBV before starting treatment with EMTRIVA. If you have HBV infection and take EMTRIVA, your HBV may get worse (flare-up) if you stop taking EMTRIVA. A "flare-up" is when your HBV infection suddenly returns in a worse way than before.
  - Do not stop taking EMTRIVA without first talking to your healthcare provider.
  - Do not run out of EMTRIVA. Refill your prescription or talk to your healthcare provider before your EMTRIVA is all gone.
  - If you stop taking EMTRIVA, your healthcare provider will need to check your health often and do blood tests regularly for several months to check your HBV infection, or give you a medication to treat hepatitis B. Tell your healthcare provider about any new or unusual symptoms you may have after you stop taking EMTRIVA.

For more information about side effects, see the section "What are the possible side effects of EMTRIVA?"

What is EMTRIVA?

EMTRIVA is a prescription medicine used in combination with other antiretroviral medicines to treat Human Immunodeficiency Virus-1 (HIV-1) infection.

HIV-1 is the virus that causes Acquired Immune Deficiency Syndrome (AIDS).

Who should not take EMTRIVA?

Do not take EMTRIVA if you are allergic to emtricitabine or any of the ingredients in EMTRIVA. See the end of this leaflet for a complete list of ingredients in EMTRIVA.

What should I tell my healthcare provider before taking EMTRIVA?

Before taking EMTRIVA, tell your healthcare provider about all of your medical conditions, including if you:

- have liver problems, including HBV infection
- have kidney problems or receive kidney dialysis treatment
- are pregnant or planning to become pregnant. It is not known if EMTRIVA can harm your unborn baby. Tell your healthcare provider if you become pregnant during treatment with EMTRIVA.
  Pregnancy Registry: There is a pregnancy registry for women who take EMTRIVA during pregnancy. The purpose of this registry is to collect information about the health of you and your baby. Talk to your healthcare provider about how you can take part in this registry.
- are breastfeeding or plan to breastfeed. EMTRIVA can pass to your baby in your breast milk. Do not breastfeed if you have HIV-1 because of the risk of passing HIV-1 to your baby. Talk with your healthcare provider about the best way to feed your baby.

Tell your healthcare provider about all the medicines you take, including prescription and over-the-counter medicines, vitamins, and herbal supplements.

Some medicines may interact with EMTRIVA. Keep a list of your medicines and show it to your healthcare provider and pharmacist when you get a new medicine.

You can ask your healthcare provider or pharmacist for a list of medicines that interact with EMTRIVA. Do not start a new medicine without telling your healthcare provider. Your healthcare provider can tell you if it is safe to take EMTRIVA with other medicines.

How should I take EMTRIVA?

- Take EMTRIVA exactly as your healthcare provider tells you to take it.
- Dosing in adults: Take EMTRIVA by mouth 1 time each day.
- Dosing in children: Take EMTRIVA by mouth 1 time each day. The child's healthcare provider will calculate the right dose of EMTRIVA (oral solution or capsule) based on the child's weight.
- EMTRIVA may be taken with or without food.
- Do not miss a dose of EMTRIVA. Missing a dose lowers the amount of medicine in your blood. Refill your EMTRIVA prescription before you run out of medicine.
- Do not change your dose or stop taking EMTRIVA without first talking with your healthcare provider. Stay under a healthcare provider's care when taking EMTRIVA.
- If you take too much EMTRIVA, call your healthcare provider or go to the nearest hospital emergency room right away.

What are the possible side effects of EMTRIVA?

EMTRIVA may cause serious side effects, including:

- See "What is the most important information I should know about EMTRIVA?"
- Changes in your immune system (Immune Reconstitution Syndrome) can happen when an HIV-infected person starts taking antiretroviral medicines. Your immune system may get stronger and begin to fight infections that have been hidden in your body for a long time. Tell your healthcare provider right away if you start having any new symptoms after starting EMTRIVA.
- Too much lactic acid in your blood (lactic acidosis). Too much lactic acid is a serious but rare medical emergency that can lead to death. Tell your healthcare provider right away if you develop any of these symptoms:

- weakness or being more tired than usual
- being short of breath or fast breathing
- cold or blue hands and feet
- fast or abnormal heartbeat

- unusual muscle pain
- stomach pain with nausea and vomiting
- feel dizzy or lightheaded

- Severe liver problems. In rare cases, severe liver problems can happen that can lead to death. Your healthcare provider may tell you to stop taking EMTRIVA if you develop new or worse liver problems during treatment with EMTRIVA. Tell your healthcare provider right away if you develop any of these symptoms:

- fatigue
- weakness
- yellowing of your skin or the white part of your eyes (jaundice)
- light colored stools

- nausea and vomiting
- confusion
- dark "tea-colored" urine
- loss of appetite for several days or longer
- stomach-area (abdominal) swelling and pain

The most common side effects of EMTRIVA include:

- headache
- diarrhea
- nausea
- tiredness
- dizziness
- depression
- problems sleeping

- abnormal dreams
- rash
- abdominal pain
- weakness
- cough
- runny nose

Skin discoloration in children may also happen with EMTRIVA.

These are not all the possible side effects of EMTRIVA.

Call your doctor for medical advice about side effects. You may report side effects to FDA at 1-800-FDA-1088.

How should I store EMTRIVA?

- Store EMTRIVA capsules at room temperature between 68°F to 77°F (20°C to 25°C) .
- Store EMTRIVA oral solution in the refrigerator between 36°F to 46°F (2°C to 8°C). Do not freeze.
- You may also store EMTRIVA oral solution at room temperature between 68°F to 77°F (20°C to 25°C) for up to 3 months. Throw away any unused EMTRIVA oral solution after 3 months.
- Keep EMTRIVA in its original container and keep the container tightly closed.
- Do not use EMTRIVA if seal over bottle opening is broken or missing.

Keep EMTRIVA and all other medicines out of reach of children.

General information about the safe and effective use of EMTRIVA.

Medicines are sometimes prescribed for purposes other than those listed in a Patient Information leaflet. Do not use EMTRIVA for a condition for which it was not prescribed. Do not give EMTRIVA to other people, even if they have the same symptoms you have. It may harm them. You can ask your healthcare provider or pharmacist for information about EMTRIVA that is written for health professionals.

What are the ingredients of EMTRIVA?

Active Ingredient: emtricitabine

Inactive Ingredients:

EMTRIVA capsules: crospovidone, magnesium stearate, microcrystalline cellulose, povidone, titanium dioxide, gelatin, and FD&C blue No. 2.

EMTRIVA oral solution: cotton candy flavor, FD&C yellow No. 6, edetate disodium, methylparaben and propylparaben, sodium phosphate (monobasic), propylene glycol, water, and xylitol. Sodium hydroxide and hydrochloric acid may be used to adjust pH.

Manufactured for and distributed by:
Gilead Sciences, Inc. Foster City, CA 94404
EMTRIVA is a trademark of Gilead Sciences, Inc., or its related companies. © 2018 Gilead Sciences, Inc. All rights reserved.
For more information, call 1-800-GILEAD-5 (1-800-445-3235).
21-500-896-GS-019

This Patient Information has been approved by the U.S. Food and Drug Administration.

Revised: December/2018

PRINCIPAL DISPLAY PANEL - Representative Bottle Label

NDC 61958-0601-1

Emtriva ®
(emtricitabine)
Capsules, 200 mg

30 capsules

Rx only

PACKAGE LABEL

PRINCIPAL DISPLAY PANEL - 170 mL Bottle Carton

NDC-61958-0602-1

Emtriva ®
(emtricitabine)
Oral Solution
10 mg/mL

170 mL

Rx only

Each mL contains
10 mg of emtricitabine

GILEAD